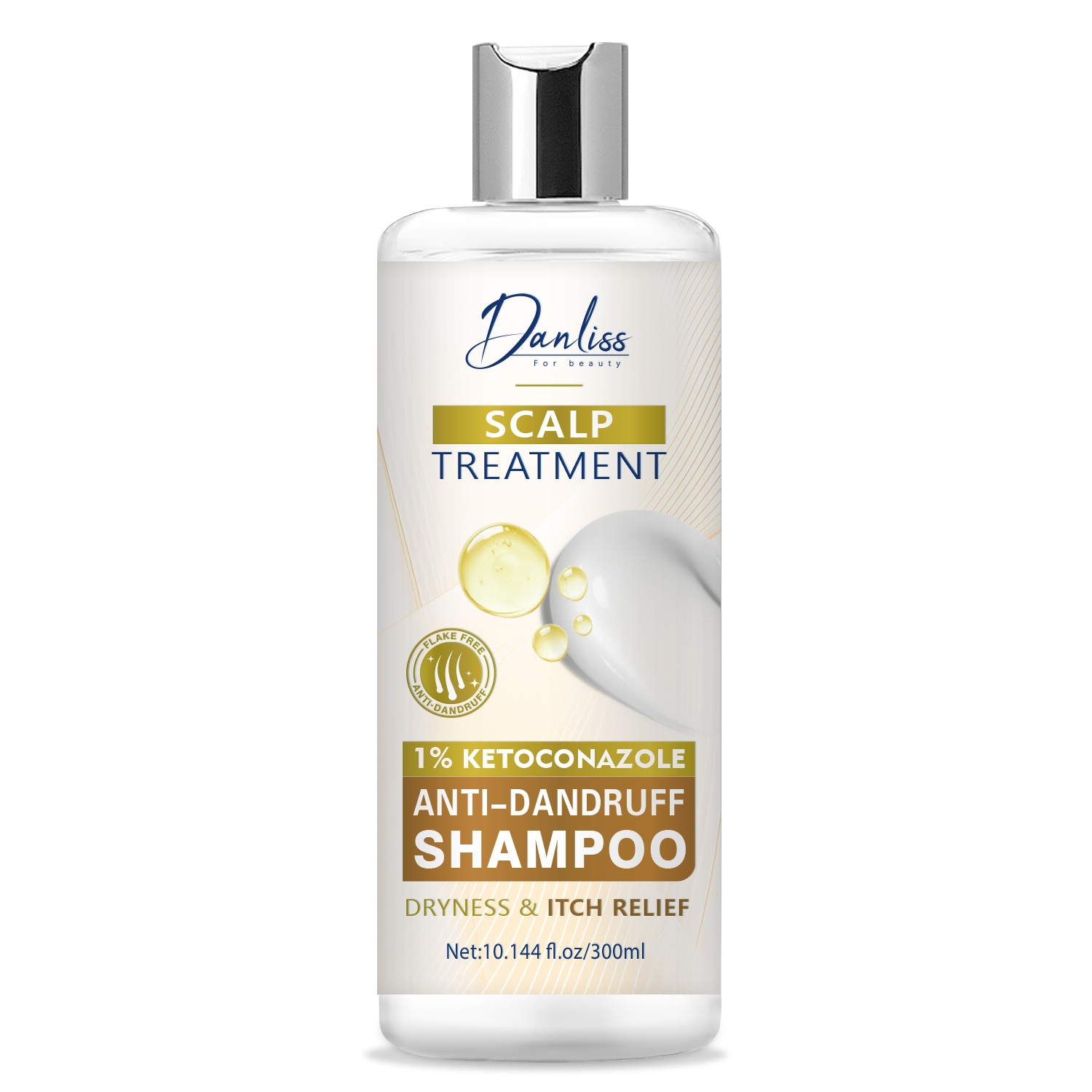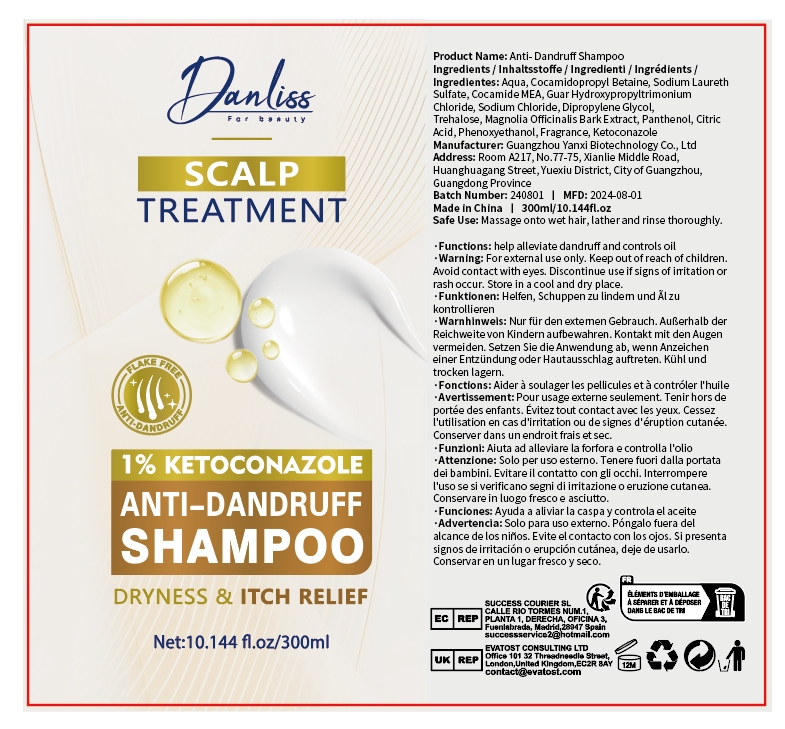 DRUG LABEL: Anti-DandruffShampoo
NDC: 84025-249 | Form: GEL
Manufacturer: Guangzhou Yanxi Biotechnology Co., Ltd
Category: otc | Type: HUMAN OTC DRUG LABEL
Date: 20241106

ACTIVE INGREDIENTS: COCAMIDE MEA 13 mg/300 mL; COCAMIDOPROPYL BETAINE 15 mg/300 mL
INACTIVE INGREDIENTS: WATER

DOSAGE AND ADMINISTRATION

Massage onto wet hair,lather and rinse thoroughly

WARNINGS

Keep out of chlidren

INACTIVE INGREDIENT

Aqua

INDICATIONS AND USAGE

For daily hair care

Keep out of children

PURPOSE

help alleviate dandriff and controls oil